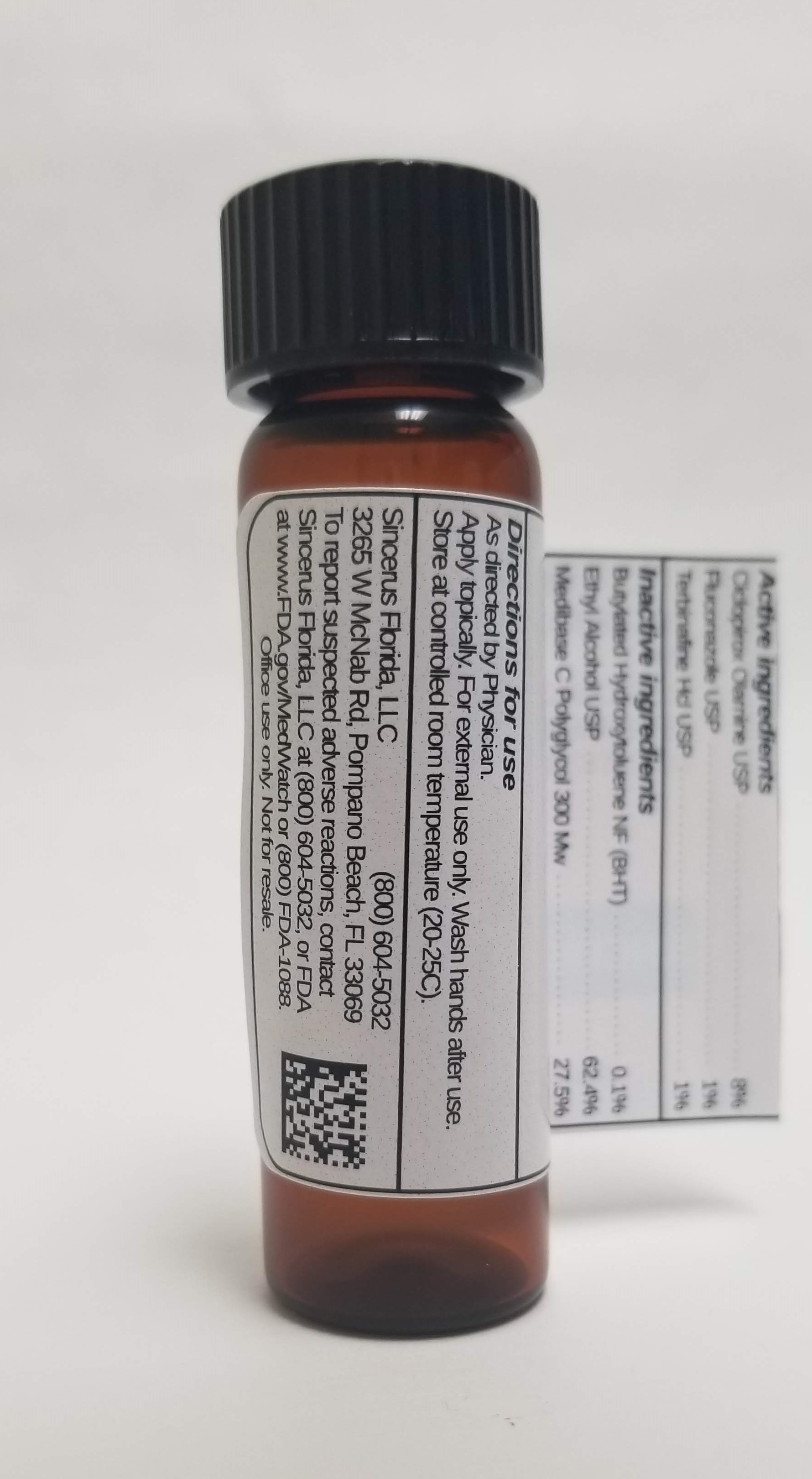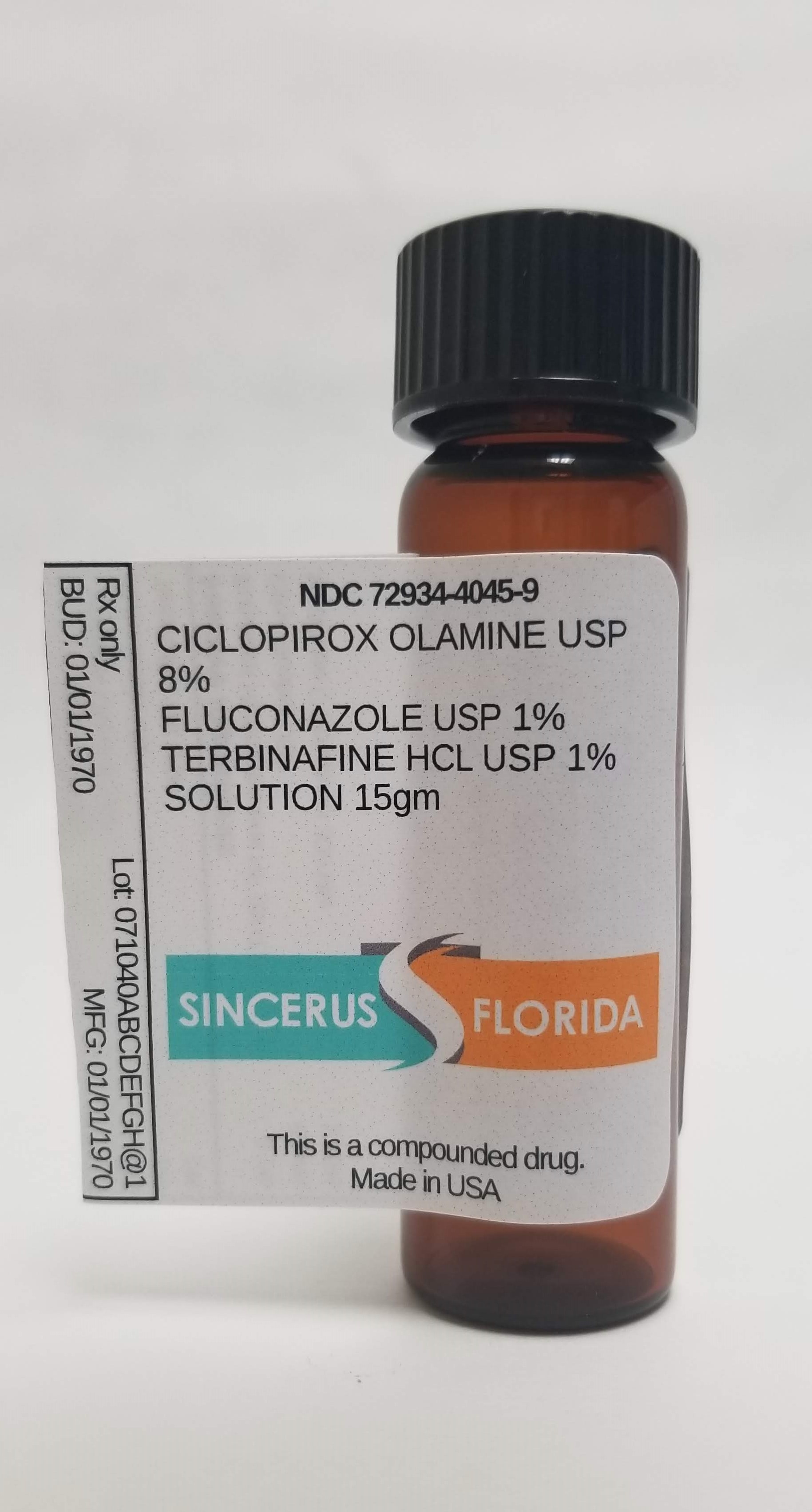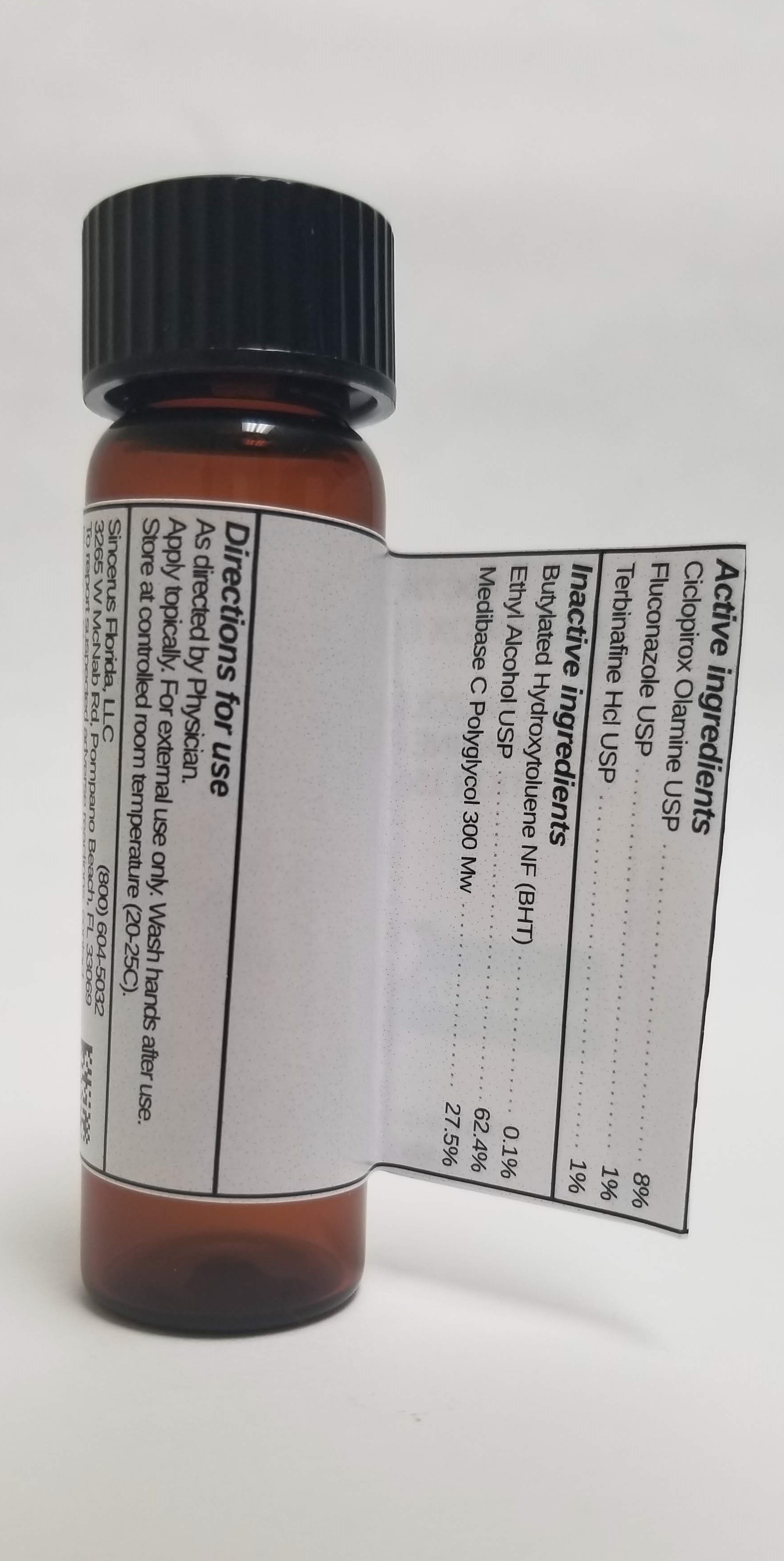 DRUG LABEL: CICLOPIROX 8% / FLUCONAZOLE 1% / TERBINAFINE HCL 1%
NDC: 72934-4045 | Form: SOLUTION
Manufacturer: Sincerus Florida, LLC
Category: prescription | Type: HUMAN PRESCRIPTION DRUG LABEL
Date: 20190424

ACTIVE INGREDIENTS: CICLOPIROX 8 g/100 g; FLUCONAZOLE 1 g/100 g; TERBINAFINE 1 g/100 g

CICLOPIROX 8% / FLUCONAZOLE 1% / TERBINAFINE HCL 1%